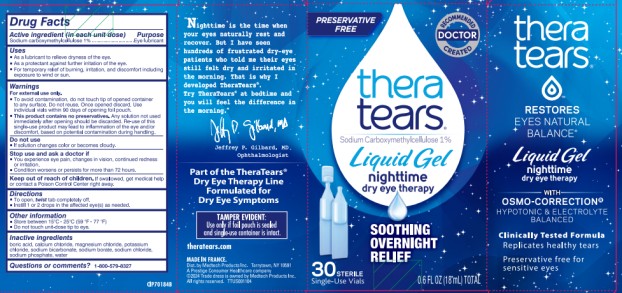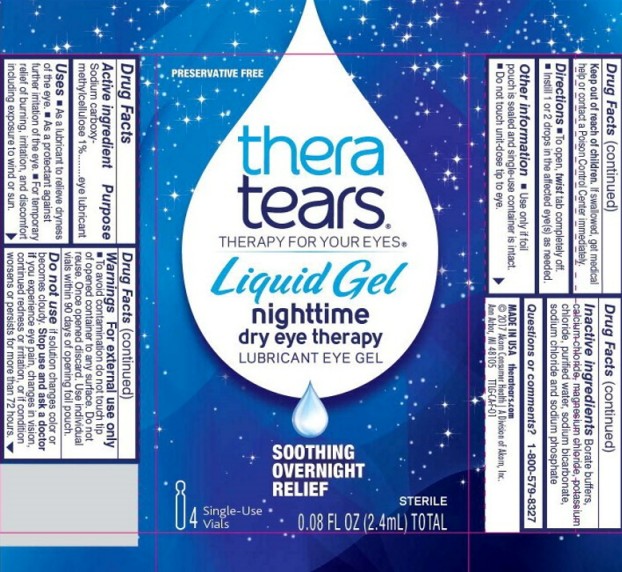 DRUG LABEL: TheraTears
NDC: 58790-002 | Form: GEL
Manufacturer: MEDTECH PRODUCTS INC
Category: otc | Type: HUMAN OTC DRUG LABEL
Date: 20251023

ACTIVE INGREDIENTS: carboxymethylcellulose sodium, unspecified form 10 mg/1 mL
INACTIVE INGREDIENTS: boric acid; sodium borate; calcium chloride; magnesium chloride; potassium chloride; water; sodium bicarbonate; sodium chloride; sodium phosphate

TheraTears Liquid Night PF 58790-003

Drug Facts

Active ingredient (In each unit dose)

sodium carboxymethylcellulose 1%

Purpose

Eye lubricant

Uses

- As a lubricant to relieve dryness of the eye.
- As a protectant against further irritation of the eye.
- For temporary relief of burning, irritation, and discomfort including exposure to wind or sun.

Warnings

For external use only

- To avoid contamination do not touch tip of opened container to any surface. Do not reuse. Once opened discard. Use individual vials within 90 days of opening foil pouch.
- This product contains no preservatives. Any solution not used immediately after opening should be discarded. Re-use of this single-use product may lead to inflammation of the eye and/or discomfort, based on potential contamination during handling.

Do not use

- If solution changes color or becomes cloudy.

Stop use and ask a doctor if

- You experience eye pain, changes in vision, continued redness or irritation.
- Condition worsens or persists for more than 72 hours.

Keep out of reach of children.

If swallowed, get medical help or contact a Poison Control Center immediately.

Directions

- To open, twist tab completely off.
- Instill 1 or 2 drops in the affected eye(s) as needed.

Other information

- Store between 15C-25C (59F-77F)
- Do not touch unit-dose tip to eye.

Inactive ingredients

boric acid, calcium chloride, magnesium chloride, potassium chloride, sodium bicarbonate, sodium borate, sodium chloride, sodium phosphate, water

Questions or comments? 1-800-579-8327

Principal Display Panel Text for Carton Label:

PRESERVATIVE

FREE

RECOMMENDED

DOCTOR

CREATED

thera

tears®

THERAPY FOR YOUR EYES®

Liquid Gel

nighttime

dry eye therapy

LUBRICANT EYE GEL

SOOTHING

OVERNIGHT

RELIEF

30 STERILE

Single-Use Vials* 0.60 FL OZ (18.0 mL) TOTAL

Principal Display Panel Text for Carton Label:

PRESERVATIVE

FREE

RECOMMENDED

DOCTOR

CREATED

thera

tears®

THERAPY FOR YOUR EYES®

Liquid Gel

nighttime

dry eye therapy

LUBRICANT EYE GEL

SOOTHING

OVERNIGHT

RELIEF

4 Single-Use Vials 0.08 FL OZ (2.4 mL) TOTAL